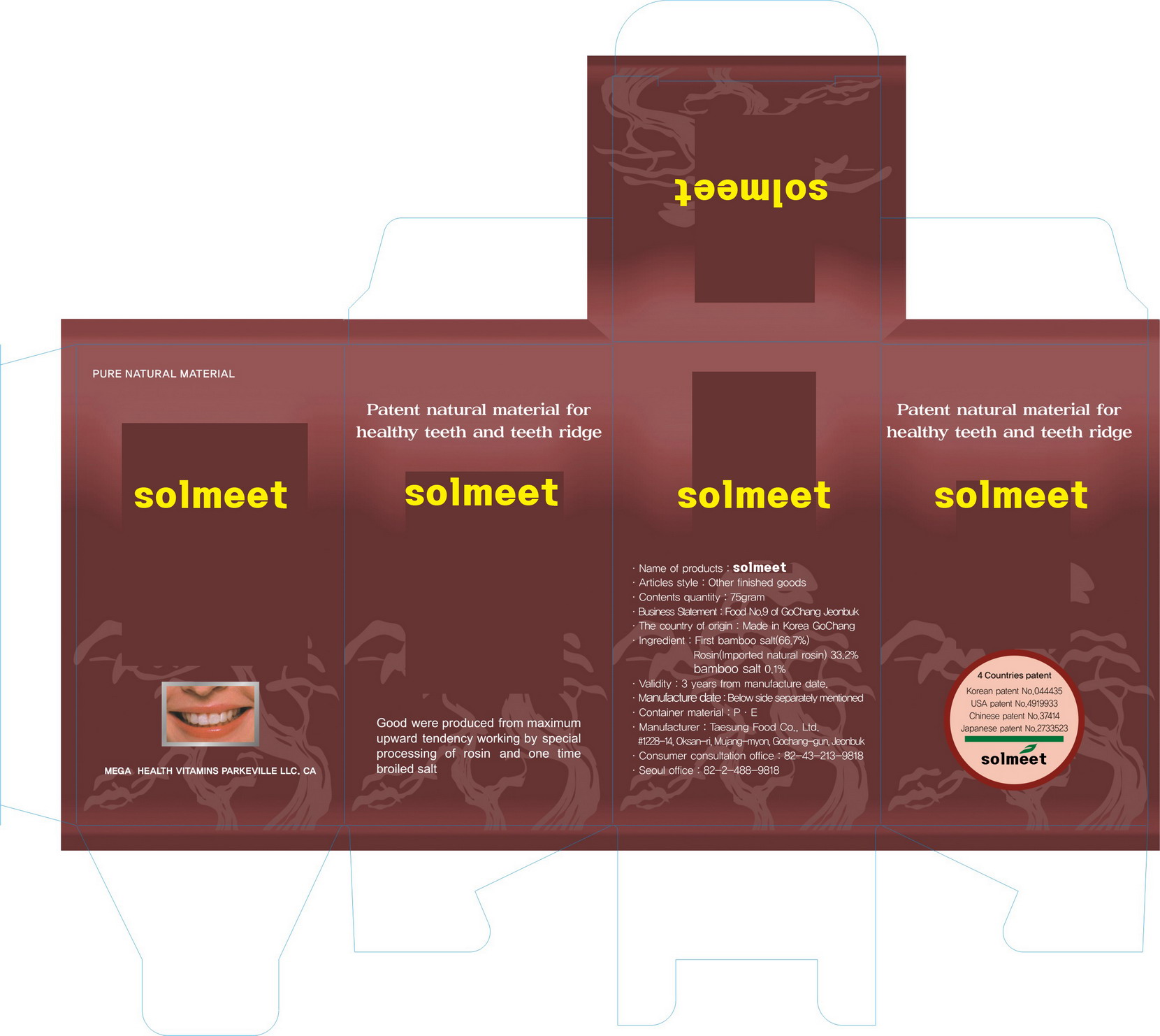 DRUG LABEL: Solmeet Denti doctor
NDC: 42352-1001 | Form: POWDER, DENTIFRICE
Manufacturer: Solbin Co., Ltd
Category: otc | Type: HUMAN OTC DRUG LABEL
Date: 20101211

ACTIVE INGREDIENTS: ROSIN 0.332 g/1 g
INACTIVE INGREDIENTS: SODIUM CHLORIDE

Drug Facts

Active Ingredient: Pine Tar

Inactive Ingredient: sodium chloride

PURPOSE

for dental care

keep out of reach of the children

INDICATIONS AND USAGE

use when is needed

WARNINGS

- do not swallow when using this product
- if more than used for rinsing is accidentally swallowed, get medical helps or contact a poison control center right away

DOSAGE AND ADMINISTRATION

Hold 1 grams in mouth for 1~2 minutes then rinse out with water